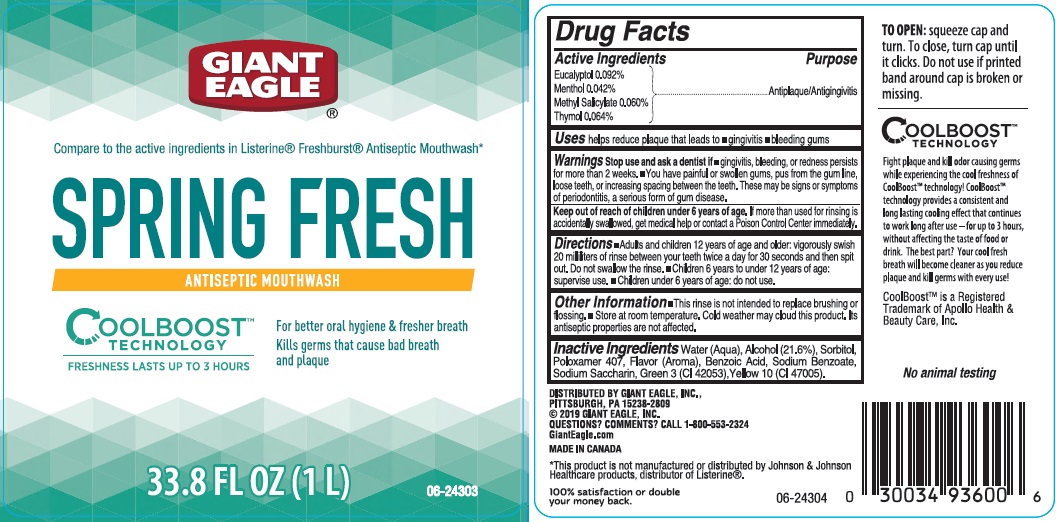 DRUG LABEL: Giant Eagle Spring Fresh Antiseptic
NDC: 63148-020 | Form: MOUTHWASH
Manufacturer: Apollo Health and Beauty Care Inc.
Category: otc | Type: HUMAN OTC DRUG LABEL
Date: 20190912

ACTIVE INGREDIENTS: EUCALYPTOL 0.92 mg/1 mL; MENTHOL 0.42 mg/1 mL; METHYL SALICYLATE 0.60 mg/1 mL; THYMOL 0.64 mg/1 mL
INACTIVE INGREDIENTS: WATER; ALCOHOL; SORBITOL; POLOXAMER 407; BENZOIC ACID; SODIUM BENZOATE; SACCHARIN SODIUM; FD&C GREEN NO. 3; D&C YELLOW NO. 10

Drug Facts

Active ingredients

Eucalyptol 0.092%

Menthol 0.042%

Methyl Salicylate 0.060%

Thymol 0.064%

Purpse

Antiplaque/Antigingivitis

Uses

helps reduce plaque that leads to

- gingivitis
- bleeding gums

Warnings

Stop use and ask a dentist if

- gingivitis, bleeding, or redness persists for more than 2 weeks.
- you have painful or swollen gums, pus from the gum line, loose teeth, or increasing spacing between the teeth. These may be signs or symptoms fo periodontitis, a serious form of gum disease.

Keep out of reach of children under 6 years of age.

If more than used for rinsing is accidentallly swallowed, get medical help or contact a Poison Control Center immediately.

Directions

- Adults and children 12 years of age and older: vigorously swish 20 milliliters of rinse between your teeth twice a day for 30 seconds and then spit out. Do not swallow the rinse.
- Children 6 years to under 12 years of age: supervise use.
- Children under 6 years of age: do not use.

Other information

- This rinse is not intended to replace brushing or flossing
- Store at room temperature. Cold weather may cloud this product. Its antiseptic properties are not affected.

Inactive ingredients

Water (Aqua), Alcohol (21.6%), Sorbitol, Poloxamer 407, Flavor (Aroma), Benzoic Acid, Sodium Benzoate, Sodium Saccharin, Green 3 (CI 42053), Yellow 10 (CI 47005).